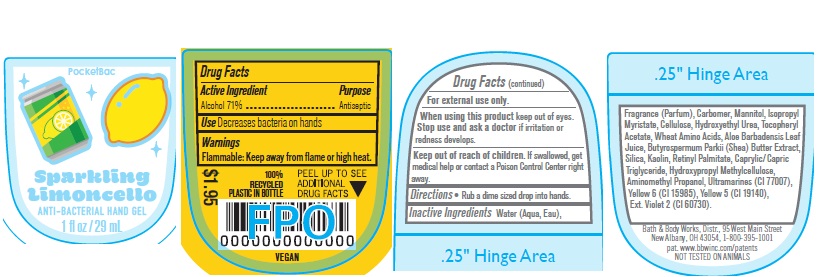 DRUG LABEL: Anti Bacterial Hand Gel
NDC: 62670-6721 | Form: GEL
Manufacturer: Bath & Body Works, Inc.
Category: otc | Type: HUMAN OTC DRUG LABEL
Date: 20241213

ACTIVE INGREDIENTS: ALCOHOL 71 mL/100 mL
INACTIVE INGREDIENTS: WATER

ABHG Sparkling Limoncello

Active Ingredient

Alcohol 71%

Purpose

Antiseptic

Use

Decreases bacteria on hands.

Warnings

Flammable: Keep away from flame or high heat.

WARNINGS

For external use only.

When using this product keep out of eyes. Stop use and ask a doctor if irritation or redness develops.

Keep out of reach of children. If swallowed, get medical help or contact a Poison Control Center right away.

Directions

Rub a dime sized drop into hands.

INACTIVE INGREDIENT

Water, Fragrance, Carbomer, Mannitol, Isopropyl Myristate, Cellulose, Hydroxyethyl Urea, Tocopheryl Acetate, Wheat Amino Acids, Aloe Barbadensis Leaf Juice, Butyrospermum Parkii (Shea) Butter Extract, Silica, Kaolin, Ultramarines, Retinyl Palmitate, Caprylic/Capric Triglyceride, Hydroxypropyl Methylcellulose, Yellow 6 (CI 15985), Yellow 5 (CI 19140), Aminomethyl Propanol, Ext. Violet 2 (CI 60730).

Bath & Body Works, Distr., 95 West Main Street
New Albany, OH 43054, 1-800-395-1001
pat. www.bbwinc.com/patents